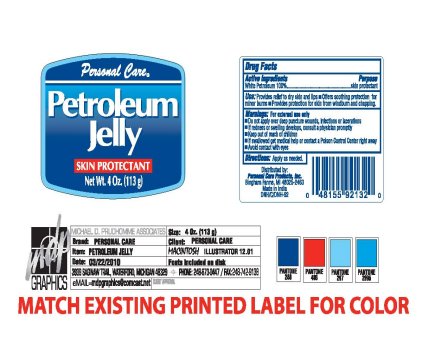 DRUG LABEL: Personal Care Petroleum Jelly Skin Protectant
NDC: 29500-8060 | Form: GEL
Manufacturer: Personal Care Products, Inc
Category: otc | Type: HUMAN OTC DRUG LABEL
Date: 20100325

ACTIVE INGREDIENTS: PETROLATUM 100 g/1 g

Personal Care Petroleum Jelly Skin Protectant

Active Ingredients Purpose

White Petroleum 100 percent...........................................Skin Protectant

PURPOSE

Use: Provides relief to dry skin and lips when used regularly

Offers soothing protection for minor burns

Provides protection for skin from windburn and chapping

Warnings: For external use only

Do not apply over deep puncture wounds, infections or lacerations

If redness or swelling develops, consult a physician promptly

Keep out of reach of children

If swallowed get medical help or contact a Poison Control Center right away

Avoid contact with eyes

DESCRIPTION

Personal Care Products, Inc.

Bingham Farms, MI 48025-2463

Made in India

INDICATIONS AND USAGE

Personal Care
Petroleum Jelly
Skin Protectant
Net Wt. 4oz (113 g)

DOSAGE AND ADMINISTRATION

Directions: Apply as needed